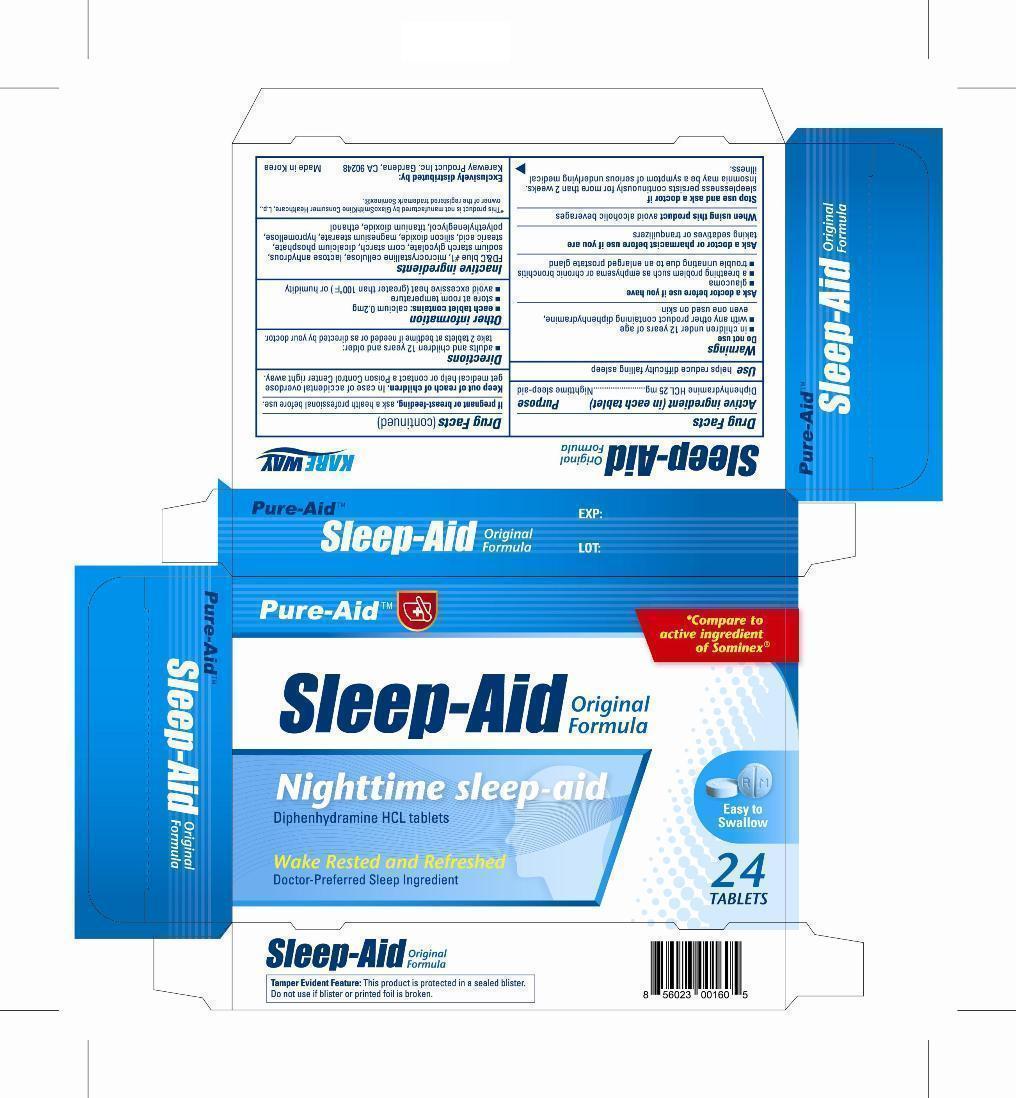 DRUG LABEL: Sleep Aid
NDC: 67510-0160 | Form: TABLET
Manufacturer: Kareway Product, Inc.
Category: otc | Type: HUMAN OTC DRUG LABEL
Date: 20130215

ACTIVE INGREDIENTS: DIPHENHYDRAMINE HYDROCHLORIDE 25 mg/1 1
INACTIVE INGREDIENTS: FD&C BLUE NO. 1; MICROCRYSTALLINE WAX; ANHYDROUS LACTOSE; SODIUM STARCH GLYCOLATE TYPE A POTATO; STARCH, CORN; DIBASIC CALCIUM PHOSPHATE DIHYDRATE; STEARIC ACID; SILICON DIOXIDE; MAGNESIUM STEARATE; HYPROMELLOSES; POLYETHYLENE GLYCOLS; TITANIUM DIOXIDE; ETHANETHIOL

Drug Facts

Active ingredient (in each tablet)

Diphenhydramine HCL 25mg

Purpose

Nighttime sleep-aid

Use

helps reduce difficulty falling asleep

Warnings

Do not use

- in children under 12 years of age
- with any other product containing diphenhydramine, even one used on skin

Ask a doctor before use if you have

- glaucoma
- a breathing problem such as emphysema or chronic bronchitis
- trouble urinating due to an enlarged prostate gland

Ask a doctor or pharmacist before use if you are

taking sedatives or tranquilizers

When using this product

avoid alcoholic beverages

Stop use and ask a doctor if

sleeplessness persists continuously for more than 2 weeks. Insomnia may be a symptom of serious underlying medical illness.

If pregnant or breast-feeding,

ask a health professional before use.

Keep out of reach of children.

In case of accidental overdose get medical help or contact a Poison Control Center right away.

Directions

- adults and children 12 years and older

take 2 tablets at bedtime if needed or as directed by your doctor.

Other information

- each tablet contains:calcium 0.2mg
- store at room temperature
- avoid excessive heat (greater than 100°F) or humidity

Inactive ingredients

FDC blue #1, microcrystalline cellulose, lactose anhydrous, sodium starch glycolate, corn starch, dicalcium phosphate, stearic acid, silcon dioxide, magnesium stearate, hypromellose, polyethyleneglycol, titanium dioxide, ethanol

Package label

Enter section text here